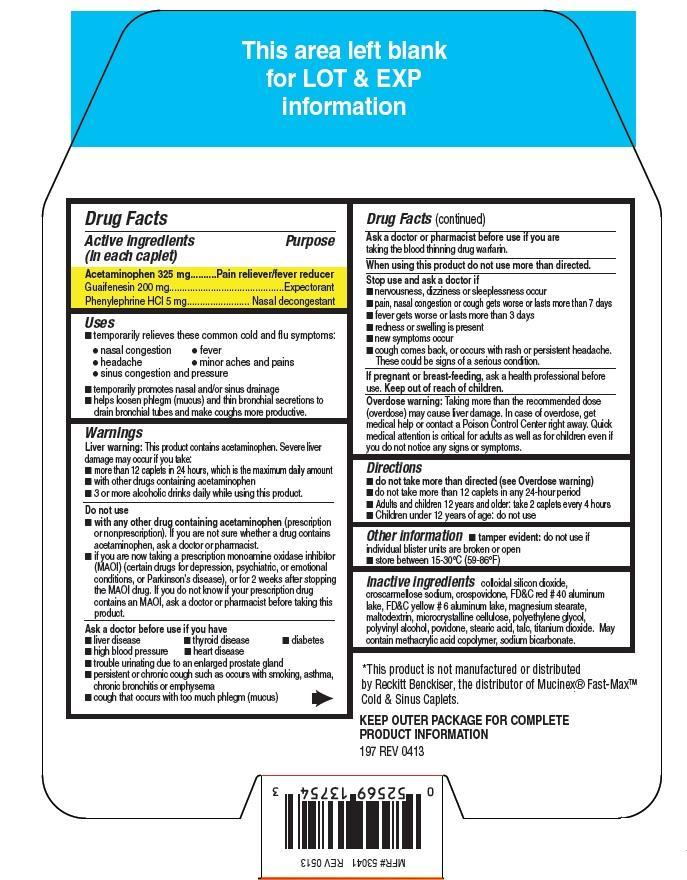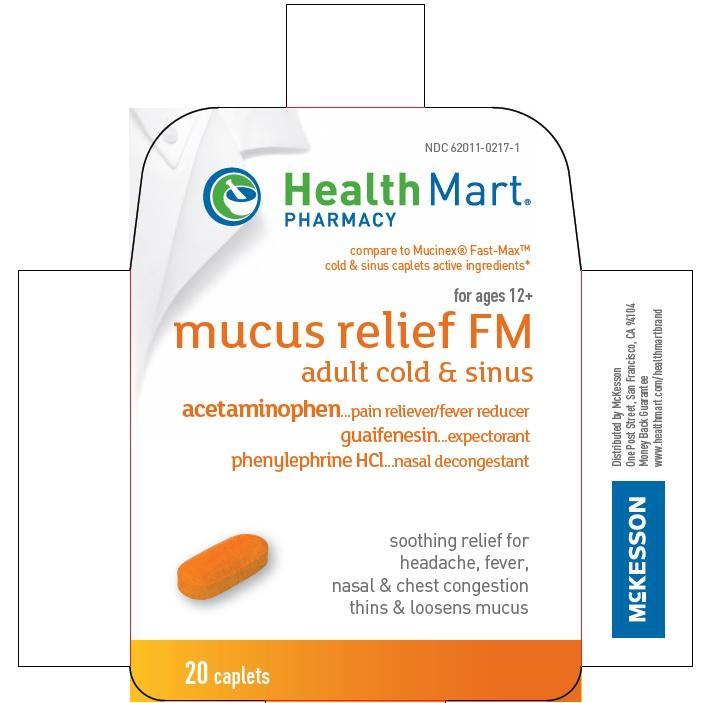 DRUG LABEL: HealthMart Mucus Relief FM
NDC: 62011-0217 | Form: TABLET
Manufacturer: Mckesson
Category: otc | Type: HUMAN OTC DRUG LABEL
Date: 20140409

ACTIVE INGREDIENTS: ACETAMINOPHEN 325 mg/1 1; GUAIFENESIN 200 mg/1 1; PHENYLEPHRINE HYDROCHLORIDE 5 mg/1 1
INACTIVE INGREDIENTS: COLLOIDAL SILICON DIOXIDE; CROSCARMELLOSE SODIUM; CROSPOVIDONE; FD&C RED NO. 40; FD&C YELLOW NO. 6; MAGNESIUM STEARATE; MALTODEXTRIN; CELLULOSE, MICROCRYSTALLINE; POLYETHYLENE GLYCOLS; POLYVINYL ALCOHOL; POVIDONE; STEARIC ACID; TALC; TITANIUM DIOXIDE

Mucus Relief FM

Active ingredients (in each caplet)

Acetaminophen 325 mg

Guaifenesin 200 mg

Phenylephrine HCl 5 mg

Purpose

Pain reliever/Fever reducer

Expectorant

Nasal decongestant

Uses

- temporarily relieves these common cold and flu symptoms:
- nasal congestion
- fever
- headache
- minor aches and pains
- sinus congestion and pressure
- temporarily promotes nasal and/or sinus drainage
- helps loosen phlegm (mucus) and thin bronchial secretions to drain bronchial tubes and make coughs more productive.

Warnings

Liver warning: This product contains acetaminophen. severe liver damage may occur if you take:

- more than 12 caplets in 24 hours, which is maximum daily amount
- with other drugs containing acetaminophen
- 3 or more alcoholic drinks daily while using this product

Do not use

- with any other drug containing acetaminophen (prescription or non prescription). If you are not sure whether a drug contains acetaminophen, ask a doctor or pharmacist.
- if you are now taking a prescription monoamine oxidase inhibitor (MAOI) (certain drugs for depression, psychiatric, or emotional conditions or parkinson's disease), or for 2 weeks after stopping the MAOI drug. If you do not know if your prescription drug contains an MAOI, ask a doctor or pharmacist before taking this product.

Ask a doctor before use if you have

- liver disease
- heart disease
- high blood pressure
- thyroid disease
- diabetes
- trouble urinating due to an enlarged prostate gland
- persistent or chronic cough such as occurs with smoking, asthma, chronic bronchitis or emphysema
- cough that occurs with too much phlegm (mucus)

Ask a doctor or pharmacist before use if

you are taking the blood thinning drug warfarin

When using this product

do not use more than directed

Stop use and ask a doctor if

- nervousness, dizziness or sleeplessness occur
- pain, nasal congestion or cough gets worse or lasts more than 7 days
- fever gets worse or lasts more than 3 days
- redness or swelling is present
- new symptoms occur
- cough comes back, or occurs with rash or persistent headache. These could be signs of a serious condition.

If pregnant or breast-feeding,

ask a health professional before use. Keep out of reach of children.

Overdose warning

Taking more than the recommended dose (overdose) may cause liver damage. In case of overdose, get medical help or contact a poison control center right away. Quick medical attention is critical for adults as well as for children even if you do not notice any signs or symptoms.

Directions

- do not take more than directed (see overdose warning)
- do not take more than 12 caplets in any 24 hour period
- Adults and children 12 years and older: take 2 caplets every 4 hours.
- Children under 12 years of age: Do not use

Other information

- tamper evident: do not use if individual blister units are borken or open
- store between 15-30oC(59-86oF)

Inactive ingredients

Colloidal silicon dioxide, croscaramellose sodium, crospovidone, FD&C red 40 aluminum lake, FD&C yellow 6 aluminum lake, magnesium stearate, maltodextrin, microcrystalline cellulose, polyethylene glycol, polyvinyl alcohol, povidone, stearic acid, talc, titanium dioxide. May contain methacrylic acid copolymer, sodium bicarbonate

PDP

Health Mart

compare to Mucinex Fast-MaxTM cold & sinus caplets active ingredients

for ages 12+

mucus relief FM

adult cold and sinus

acetaminophen.....pain reliever/Fever reducer

guaifenesin....expectorant

phenylephrine HCl.....nasal congestion

soothing relief for headache, fever, nasal and chest congestion

thins and loosens mucus

20 Caplets